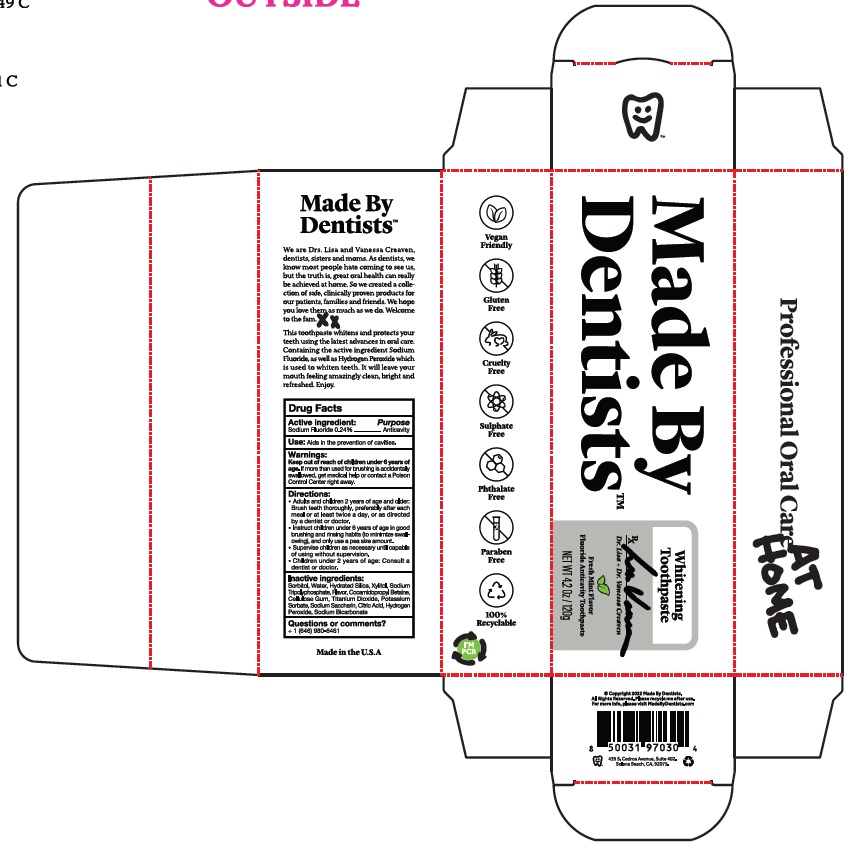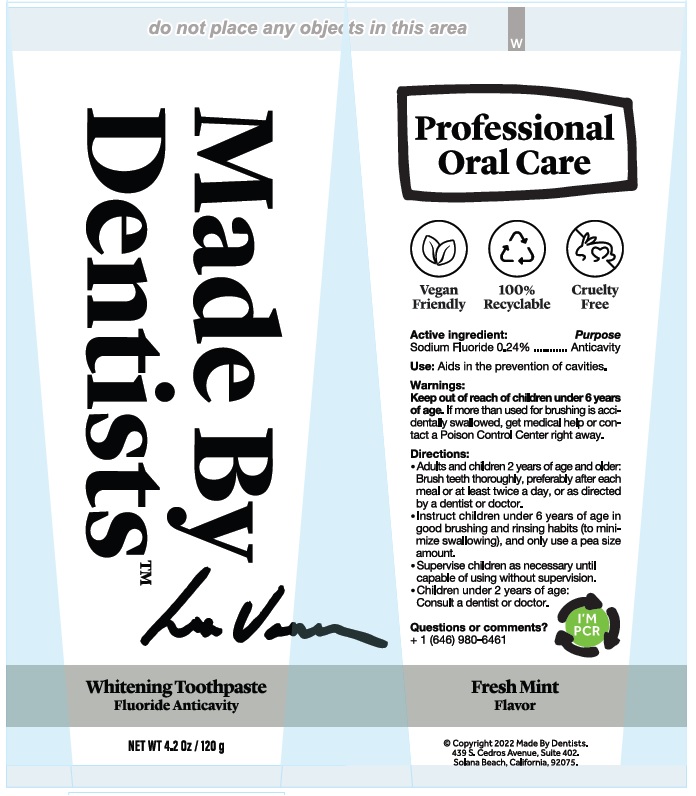 DRUG LABEL: Made By Dentists, Inc.  Whitening
NDC: 75065-017 | Form: PASTE
Manufacturer: Made By Dentists, Inc.
Category: otc | Type: HUMAN OTC DRUG LABEL
Date: 20251208

ACTIVE INGREDIENTS: SODIUM FLUORIDE 0.24 g/100 g
INACTIVE INGREDIENTS: SORBITOL; WATER; HYDRATED SILICA; XYLITOL; SODIUM TRIPOLYPHOSPHATE ANHYDROUS; COCAMIDOPROPYL BETAINE; CARBOXYMETHYLCELLULOSE SODIUM, UNSPECIFIED; TITANIUM DIOXIDE; POTASSIUM SORBATE; SACCHARIN SODIUM; CITRIC ACID MONOHYDRATE; HYDROGEN PEROXIDE; SODIUM BICARBONATE

Made By Dentists Whitening Toothpaste

Drug Facts

Active ingredient:

Sodium Fluoride 0.24%

Purpose Anticavity

INDICATIONS AND USAGE

Use: Aids in the prevention of cavities.

Warnings:

Keep out of reach of children under 6 years of age.If
more than used for brushing is accidentally swallowed, get
medical help or contact a Poison Control Center right away.

Directions:
• Adults and children 2 years of age and older:
Brush teeth thoroughly, preferably after each
meal or at least twice a day, or as directed
by a dentist or doctor.
• Instruct children under 6 years of age in good
Brushing and rinsing habits (to minimize swall-
owing), and only use a pea size amount
• Supervise children as necessary until capable
of using without supervision.
• Children under 2 years of age: Consult a
dentist or doctor.

Inactive Ingredients:
Sorbitol, Water, Hydrated Silica, Xylitol, Sodium
Tripolyphosphate, Flavor, Cocamidopropyl Betaine,
Cellulose Gum, Titanium Dioxide, Potassium
Sorbate, Sodium Saccharin, Citric Acid, Hydrogen
Peroxide, Sodium Bicarbonate

Questions? +1 (646) 980-6461

Whitening Toothpaste Product Labeling

Whitening Toothpaste

Made By Dentists™

NET WT 4.2 Oz / 120g

MADE IN THE USA

@Copyright: 2022 Made By Dentists

439 S. Cedros Avenue, Suite 402.

Solana Beach, CA, 92075

Carton

Tube

res